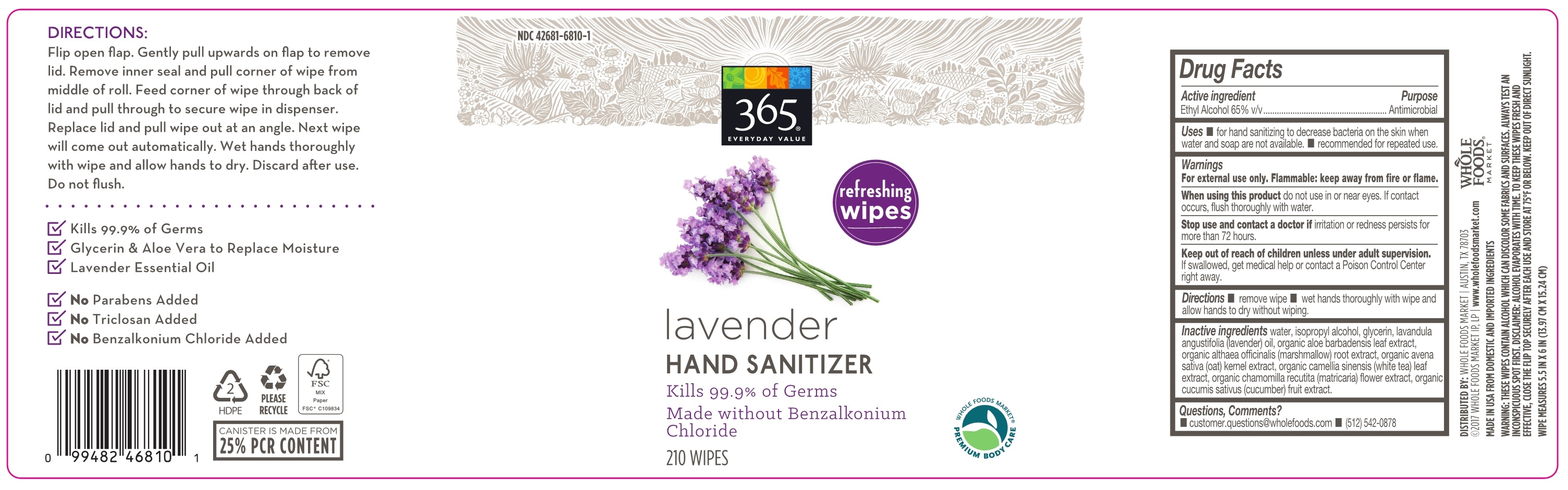 DRUG LABEL: Lavender Hand Sanitizing Wipes
NDC: 42681-6810 | Form: CLOTH
Manufacturer: Whole Foods Market, Inc.
Category: otc | Type: HUMAN OTC DRUG LABEL
Date: 20180608

ACTIVE INGREDIENTS: ALCOHOL 65 mL/100 mL
INACTIVE INGREDIENTS: ISOPROPYL ALCOHOL; LAVENDER OIL; GLYCERIN; ALOE VERA LEAF; CUCUMBER; CHAMOMILE; OAT; ALTHAEA OFFICINALIS ROOT

Active Ingredient

Ethyl Alcohol 65% V/V

Purpose

Antimicrobial

Uses

- for hand sanitizing to decrease bacteria on skin when water and soap are not available.
- recommended for repeated use.

Warnings

For external use only. Flammable: keep away from fire or flame. When using this product do not use in or near eyes. If contact occurs, flush thoroughly with water. Stop use and contact a doctor if irritation or redness persists for more than 72 hours.

Keep out of reach of children unless under adult supervision. If swallowed, get medical help or contact a Poison Control Center right away.

Directions

- remove wipe
- wet hands thoroughly with wipe and allow hands to dry without wiping

Inactive ingredients

Water, Isopropyl Alcohol, Glycerin, Lavandula Angustifolia (Lavender) Oil, Organic Aloe Barbadensis Leaf Extract, Organic Althaea Officinalis Root Extract, Organic Avena Sativa (Oats) Extract, Organic Camellia Sinensis (White Tea) Leaf Extract, Organic Chamomilla Recutita (Matricaria) Flower Extract, Organic Cucumis Sativus (Cucumber) Fruit Extract

Questions, Comments?

- Customer.questions@wholefoods.com
- (512)542-0878